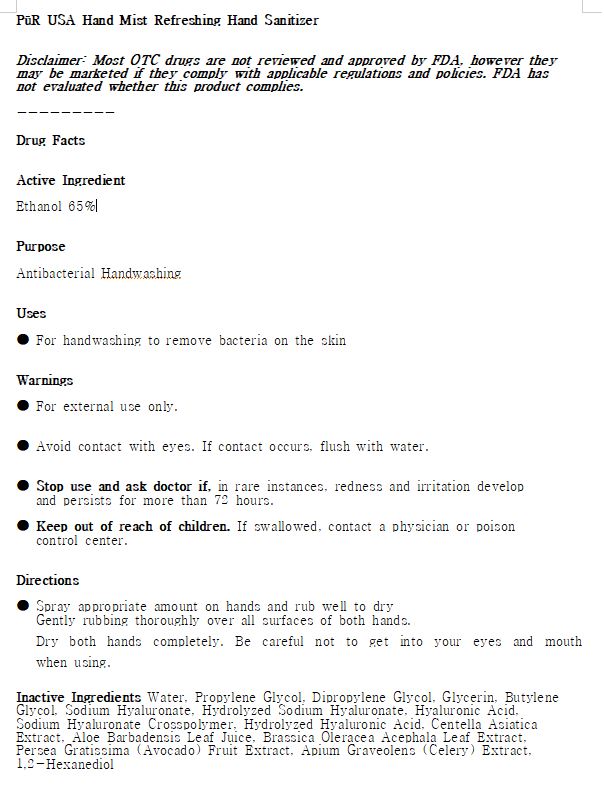 DRUG LABEL: PUR USA Hand Mist Refreshing Hand Sanitizer
NDC: 77098-0002 | Form: LIQUID
Manufacturer: MESO PHARM CO LTD
Category: otc | Type: HUMAN OTC DRUG LABEL
Date: 20200430

ACTIVE INGREDIENTS: ALCOHOL 65 mL/100 mL
INACTIVE INGREDIENTS: BUTYLENE GLYCOL; GLYCERIN; HYALURONATE SODIUM; ALOE VERA LEAF; WATER

Drug Facts

ACTIVE INGREDIENT

alcohol

INACTIVE INGREDIENT

Water, Propylene Glycol, Dipropylene Glycol, Glycerin, Butylene Glycol, Sodium Hyaluronate, Hydrolyzed Sodium Hyaluronate, Hyaluronic Acid, Sodium Hyaluronate Crosspolymer, Hydrolyzed Hyaluronic Acid, Centella Asiatica Extract, Aloe Barbadensis Leaf Juice, Brassica Oleracea Acephala Leaf Extract, Persea Gratissima (Avocado) Fruit Extract, Apium Graveolens (Celery) Extract, 1,2-Hexanediol

PURPOSE

Sterilization of hands and skin

KEEP OUT OF REACH OF THE CHILDREN

INDICATIONS AND USAGE

Apply to clean, dry hands. Apply sufficient amount to thoroughly wet all surfaces of hands and fingers. Rub onto hands until dry.

Supervise children in the use of this product.

WARNINGS

■ Flammable. Keep away from fire or flame.

■ For external use only.

■ Do not use in eyes.

■ lf swallowed, get medical help promptly.

■ Stop use, ask doctor lf irritation occurs.

■ Keep out of reach of children.

DOSAGE AND ADMINISTRATION

for external use only